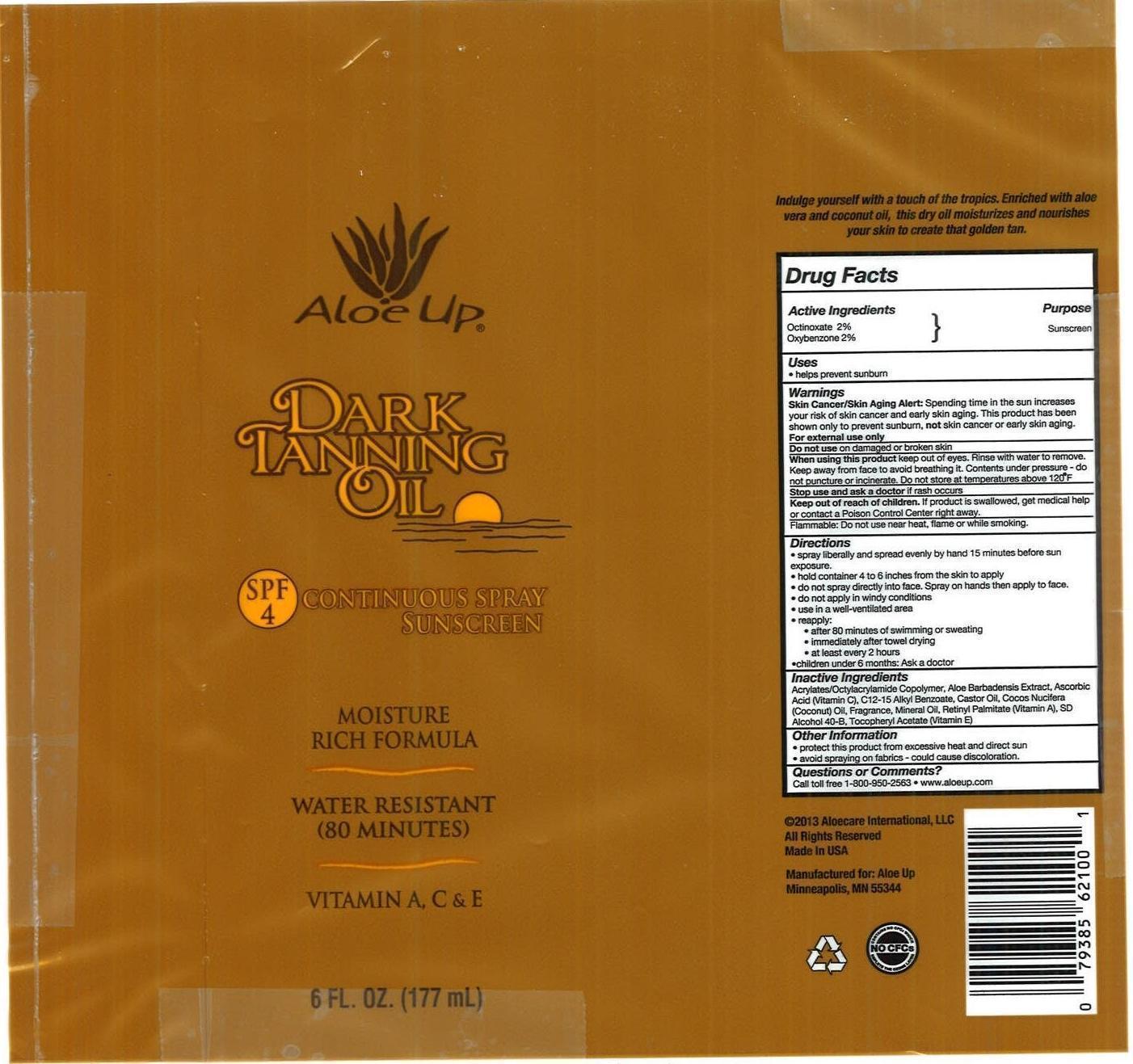 DRUG LABEL: Aloe Up
NDC: 13630-0041 | Form: SPRAY
Manufacturer: Prime Packaging, Inc.
Category: otc | Type: HUMAN OTC DRUG LABEL
Date: 20200117

ACTIVE INGREDIENTS: OCTINOXATE 16.6 mg/1 mL; OXYBENZONE 16.6 mg/1 mL
INACTIVE INGREDIENTS: ASCORBIC ACID; CASTOR OIL; MINERAL OIL; COCONUT OIL; ALOE VERA LEAF; VITAMIN A PALMITATE; ALCOHOL; .ALPHA.-TOCOPHEROL ACETATE; ALKYL (C12-15) BENZOATE

Active ingredients

Octinoxate 2 %, and Oxybenzone 2 %

Purpose

Sunscreen

Uses

- helps prevent sunburn

Warnings

Skin Cancer/Skin Aging Alert: Spending time in the sun increases your risk of skin cancer and early skin aging. This product has been shown only to prevent sunburn, not skin cancer or early skin aging.

OTHER SAFETY INFORMATION

For external use only

Do not use on damaged or broken skin.

When using this product keep out of eyes. Rinse with water to remove. Keep away from face to avoid breathing it. Contents under pressure - do not puncture or incinerate. Do not store at temperatures above 120oF

Stop use and ask a doctor if rash occurs.

Keep out of reach of children. If product is swallowed, get medical help or contact a Poison Control Center right away.

OTHER SAFETY INFORMATION

Flammable: Do not use near heat, flame or while smoking.

Directions

- spray liberally and spread by hand 15 minutes before sun exposure
- hold container 4 to 6 inches from the skin to apply
- do not spray directly into face. Spray on hands then apply to face.
- do not apply in windy condiions
- use in well-ventillated area
- reapply:
  - after 80 minutes of swimming or sweating
  - immediately after towel drying
  - at least every 2 hours
- children under 6 months: Ask a doctor

Inactive Ingredients

Acrylates/Octylacrylamide Copolymer, Aloe Barbadensis Extract, Ascorbic Acid, C12-15 Alkyl Benzoate, Castor Oil, Cocos Nucifera (Coconut) Oil, Fragrance (Parfum), Mineral Oil, Retinyl Palmitate, SD Alcohol 40-B (Alcohol Denat.), Tocopheryl Acetate

Other information

- protect this product from excesive heat and direct sun
- avoid spraying on fabrics - could cause discoloration

Questions or Comments?

Call toll free 1-800-950-2563 - www.aloeup.com

PRINCIPAL DISPLAY PANEL - 177 mL Can Label

Aloe Up
DARK

TANNING

OIL

SPF

4

CONTINUOUS SPRAY

SUNSCREEN

MOISTURE

RICH FORMULA

WATER RESISTANT

(80 MINUTES)

VITAMIN A, C & E

6 FL OZ (177 mL)